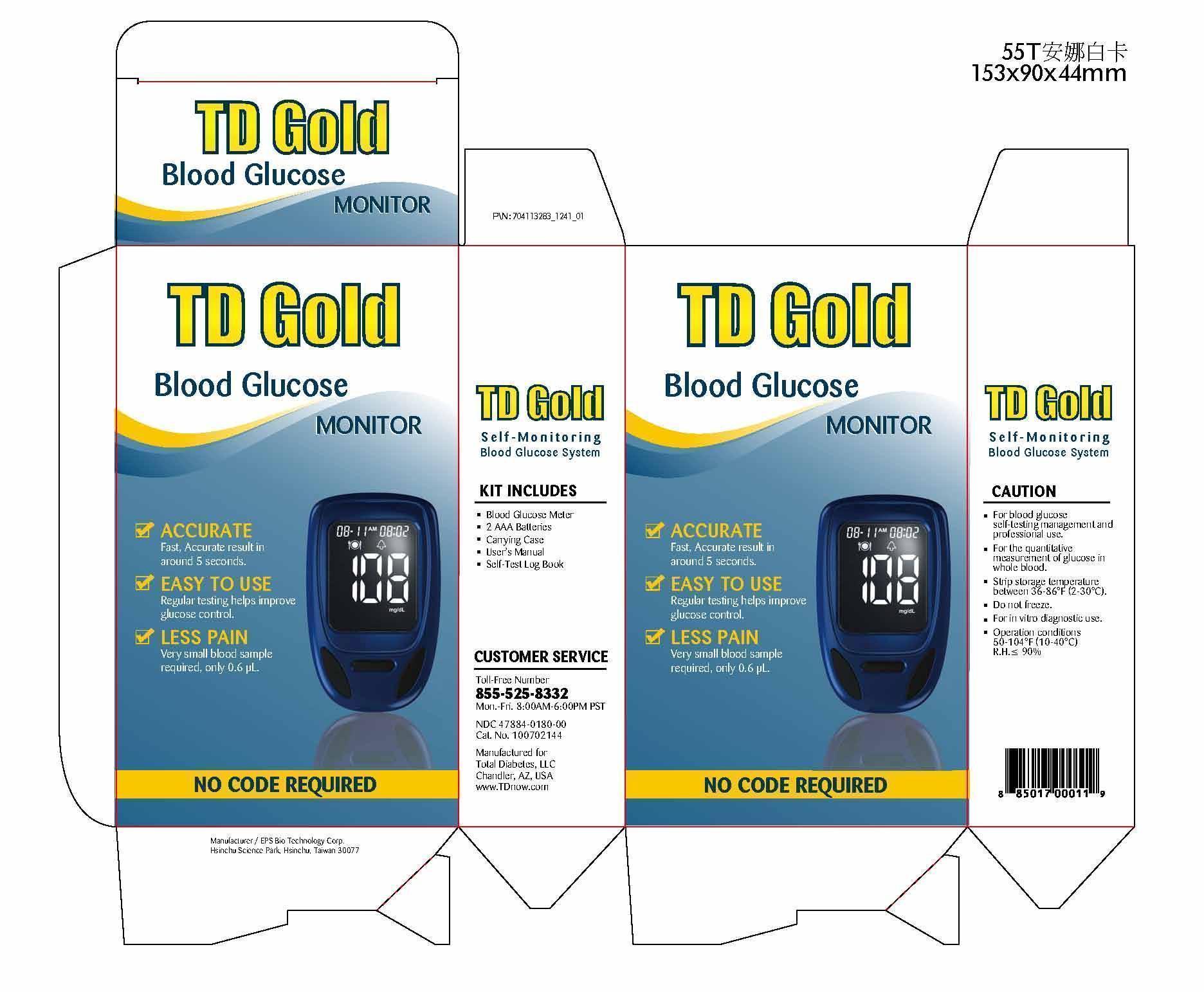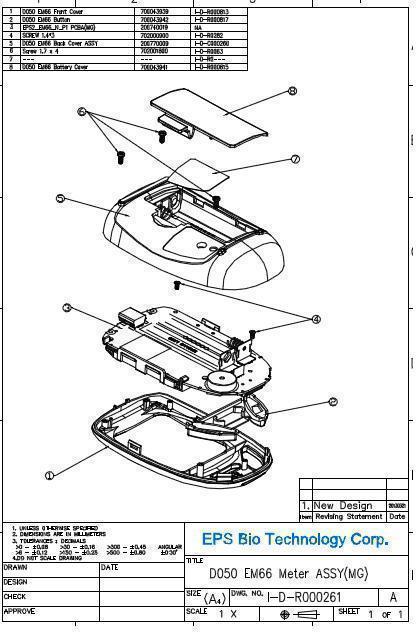 DRUG LABEL: TD GOLD KIT SET E
NDC: 47884-180
Manufacturer: EPS Bio Technology Corp.
Category: other | Type: MEDICAL DEVICE
Date: 20130830

Home Use Medical Device: TD Gold Self-monitoing Blood Glucose System